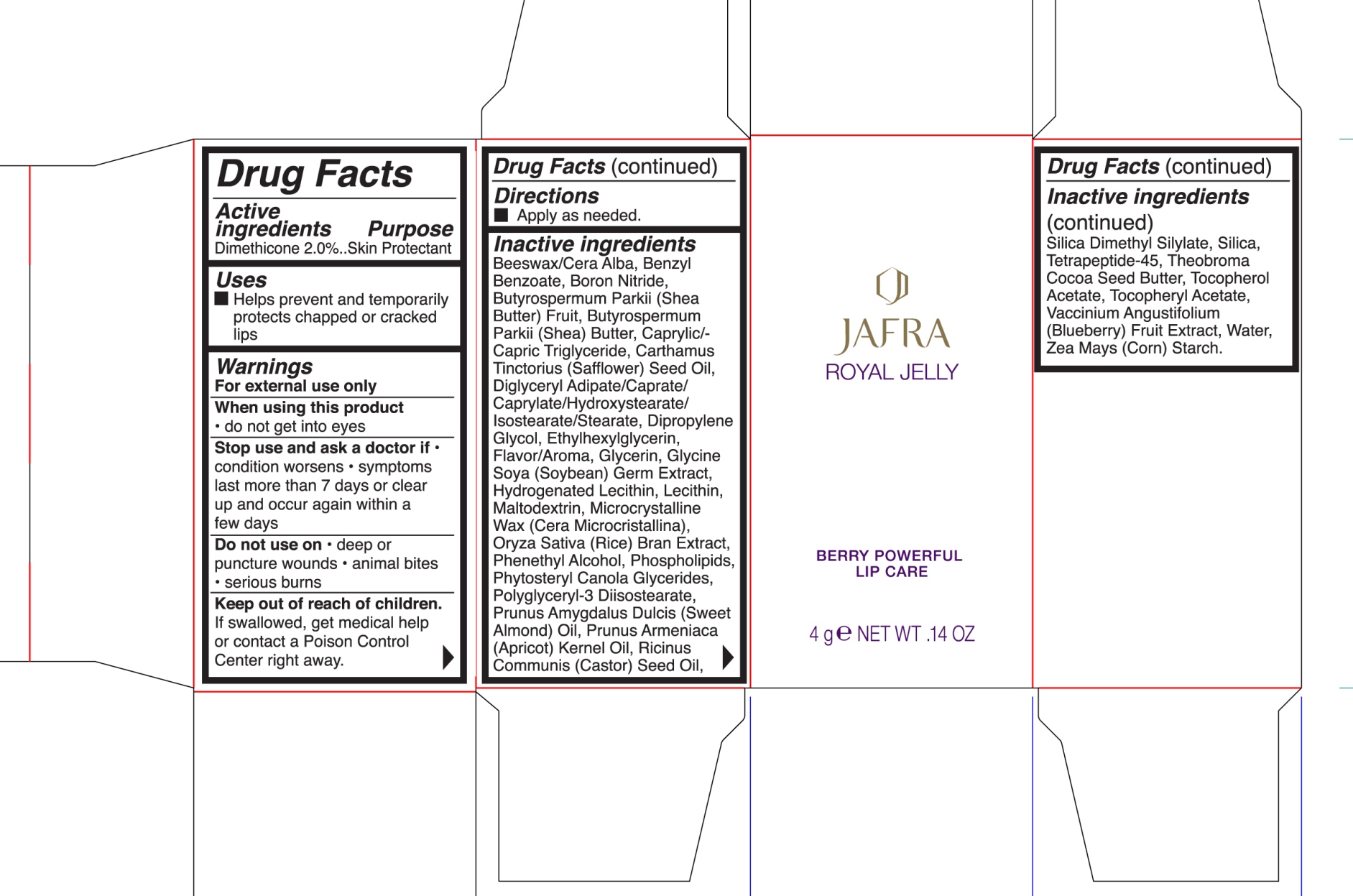 DRUG LABEL: Berry Powerful Lip Care
NDC: 68828-278 | Form: JELLY
Manufacturer: JAFRA COSMETICS INTERNATIONA
Category: otc | Type: HUMAN OTC DRUG LABEL
Date: 20200622

ACTIVE INGREDIENTS: DIMETHICONE 2 g/100 g
INACTIVE INGREDIENTS: BENZYL BENZOATE; BORON NITRIDE; SHEA BUTTER; MEDIUM-CHAIN TRIGLYCERIDES; SAFFLOWER OIL; DIPROPYLENE GLYCOL; ETHYLHEXYLGLYCERIN; GLYCERIN; SOYBEAN GERM; HYDROGENATED SOYBEAN LECITHIN; LECITHIN, SOYBEAN; MALTODEXTRIN; MICROCRYSTALLINE WAX; RICE BRAN; PHENYLETHYL ALCOHOL; POLYGLYCERYL-3 DIISOSTEARATE; ALMOND OIL; APRICOT KERNEL OIL; CASTOR OIL; SILICA DIMETHYL SILYLATE; SILICON DIOXIDE; COCOA BUTTER; .ALPHA.-TOCOPHEROL ACETATE; LOWBUSH BLUEBERRY; WATER; STARCH, CORN

Royal Jelly Berry Powerful Lip Care

Active ingredient Purpose

Dimethicone 2.0% Skin protectant

Uses

Helps prevent and temporarily chapped or cracked lips

Keep out of reach of children. If swallowed, get medical help or contact a Poison Control Center right away.

Stop use and ask a doctor if

- condition worsens
- symptoms last more than 7 days or clear up and occur again within a few days

Warnings

For external use only

When using this product do not get into eyes

Do not use deep on

- Deep puncture wounds
- Animal Bites
- Serious burns

Directions

Apply as needed.

Inactive ingredients

Beeswax/Cera Alba, Benzyl Benzoate, Boron Nitride, Butyrospermum Parkii (Shea) Butter, Caprylic/Capric Triglyceride, Carthamus Tinctorius (Safflower) Seed Oil, Diglyceryl Adipate/Caprate/Caprylate/Hydroxystearate/Isostearate/Stearate, Dipropylene Glycol, Ethylhexylglycerin, Flavor/Aroma, Glycerin, Glycine Soya (Soybean) Germ Extract, Hydrogenated Lecithin, Lecithin, Maltodextrin, Microcrystalline Wax (Cera Microcrystallina), Oryza Sativa (Rice) Bran Extract, Phenethyl Alcohol, Phospholipids, Phytosteryl Canola Glycerides, Polyglyceryl-3 Diisostearate, Prunus Amygdalus dulcis (sweet Almond) Oil. Prunus Armeniaca (Apricot) Kernel Oil, Ricinus Communis (castor) seed Oil, Silica Dimethyl Silylate, Silica, Terapeptide-45, Theobroma Cocoa Seed Butter, Tocopherol Acetate, Vaccinium Angustifolium (Blueberry) Fruit Extract, Water, Zea Mays (Corn) Starch.

PACKAGE LABEL

Jafra Royal Jelly

Berry Powerful Lip Care

4 g NET WT .14 oz